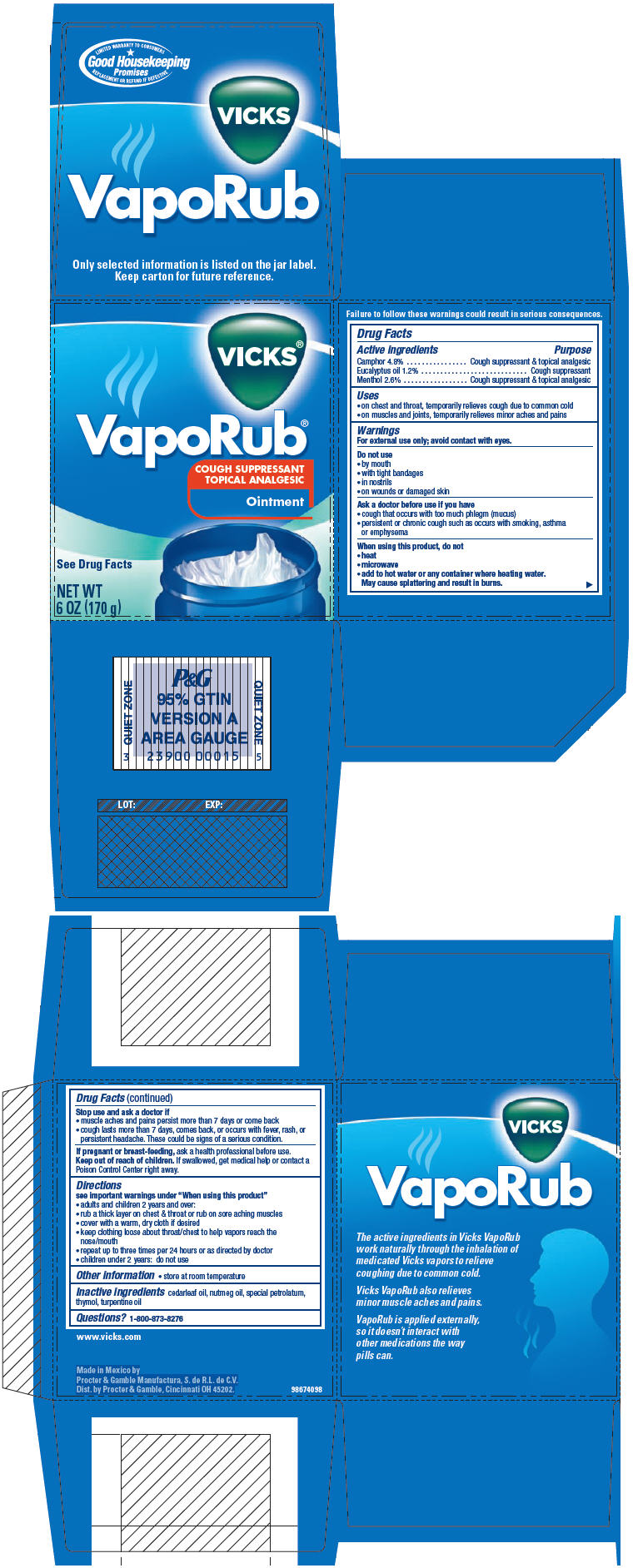 DRUG LABEL: Vicks Vaporub
NDC: 69772-390 | Form: OINTMENT
Manufacturer: Genesis Imports & Exports
Category: otc | Type: HUMAN OTC DRUG LABEL
Date: 20171228

ACTIVE INGREDIENTS: EUCALYPTUS OIL 0.012 g/1 g; CAMPHOR (SYNTHETIC) 0.048 g/1 g; MENTHOL 0.026 g/1 g
INACTIVE INGREDIENTS: CEDAR LEAF OIL; NUTMEG OIL; THYMOL; TURPENTINE OIL

Active Ingredients:

Camphor 4.8 %

Eucalyptus oil 1.2%

Menthol 2.63%

PURPOSE

Cough suppressant & topical analgesic,

Cough suppressant

DOSAGE AND ADMINISTRATION

* On Chest and throat, temporarily relieves cough due to common cold

* On Muscles and joins, temporarily relieves minor aches and pains

Warnings

For external use only; avoid contact with eyes.

Do Not Use

* By mouth

*With tight bandages

*In nostrils

*On wounds or damaged skin

Ask A doctor use if you have:

*cough that occurs with too much phlegm (mucus)

*Persistent or chronic such as occurs with smoking, asthma or emplysema

When use this product, do not

* HEat

* Microware

* Add to hot water or any container where heating water.

May cause splattering and result in burns

PREGNANCY OR BREAST FEEDING

If pregnant or breast-feeding, ask a health professional before use

Keep Out Of reach of children

Directions:

See important warnings under when using this product

- adults and children 2 years and over:

1. RUB A THICK LAYER ON CHEST & THROAT OR RUB ON SORE ACHING MISCLES
2. Cover with a warm, dry cloth if desired
3. Keep clothing loose abouth throat/chest to help vapors reach the nose/ mouse
4. repeat up three times per 24 hours or as directed by doctor
5. children under 2 yearsL do not use.

Inactive ingredients:

Cedarleaf oil, nutmeg oil, special petrolatum, thymol, turpentine oil.